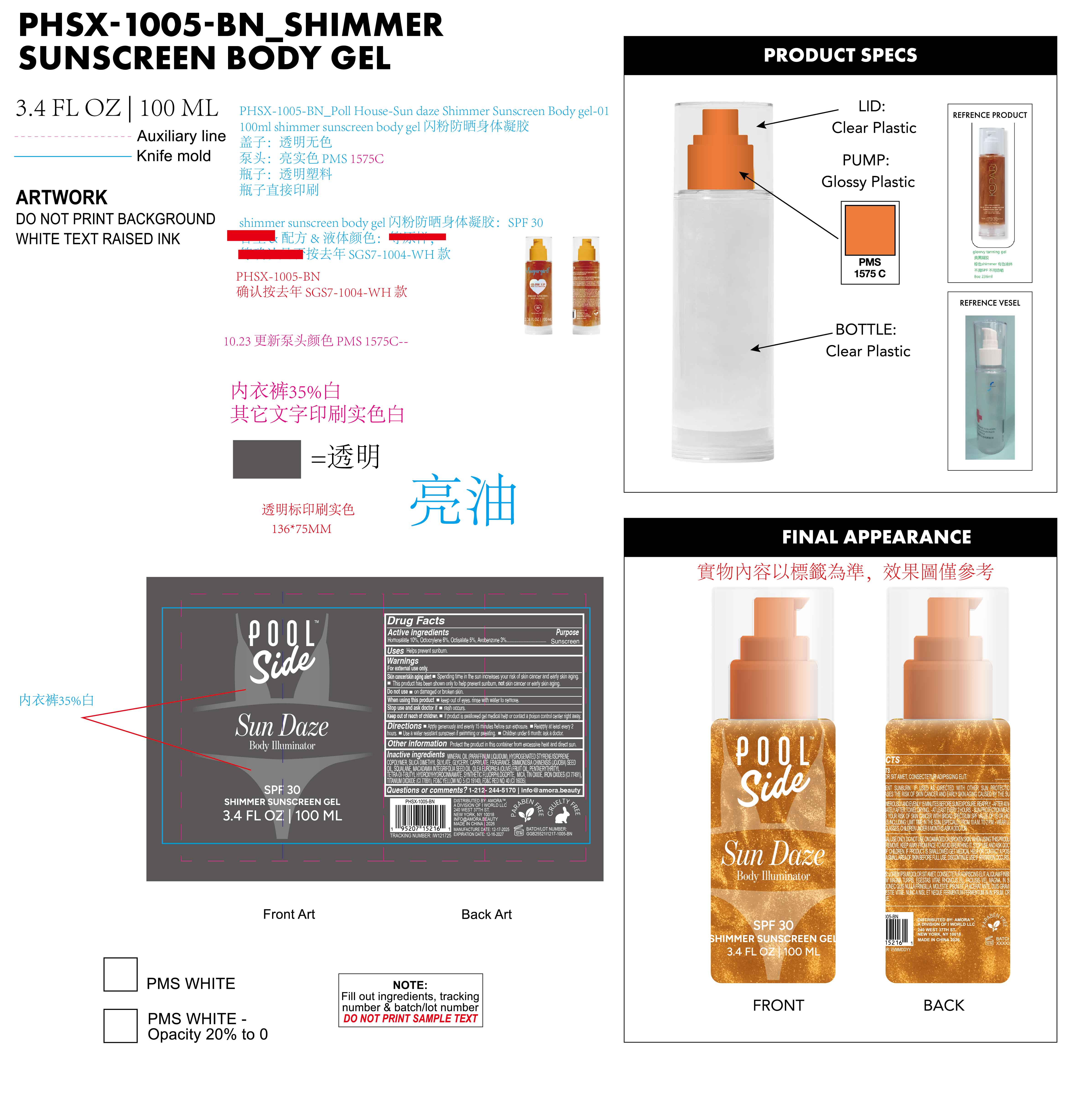 DRUG LABEL: Poolside Sun Daze Body Illuminator SPF 30 shimmer sunscreen gel
NDC: 85161-163 | Form: GEL
Manufacturer: Longway Technology(Guangzhou)Co.,Ltd.
Category: otc | Type: HUMAN OTC DRUG LABEL
Date: 20251204

ACTIVE INGREDIENTS: AVOBENZONE 0.03 g/1 mL; HOMOSALATE 0.1 g/1 mL; OCTOCRYLENE 0.06 g/1 mL; OCTISALATE 0.05 g/1 mL
INACTIVE INGREDIENTS: FRAGRANCE 13576; MAGNESIUM POTASSIUM ALUMINOSILICATE FLUORIDE; STYRENE/ISOPRENE COPOLYMER (28:72; 210000 MW); SQUALANE; TIN OXIDE; MINERAL OIL; SIMMONDSIA CHINENSIS (JOJOBA) SEED OIL; SILICA DIMETHYL SILYLATE; OLEA EUROPAEA (OLIVE) FRUIT OIL; CI 19140; CI 16035; PENTAERYTHRITYL TETRA-DI-T-BUTYL HYDROXYHYDROCINNAMATE; CI 77491; MICA; CI 77891; MACADAMIA INTEGRIFOLIA SEED OIL; GLYCERYL CAPRYLATE

ACTIVE INGREDIENT

Homosalate 10%, Octocrylene 6%, Octisalate 5%, Avobenzone 3%.

PURPOSE

Sunscreen

OTHER SAFETY INFORMATION

Protect the product in this container from excessive heat and direct sun.

QUESTIONS

1-212- 244-5170 | info@amora.beauty

INDICATIONS AND USAGE

Helps prevent sunburn.

WARNINGS

For external use only.

Spending time in the sun increases your risk of skin Skin cancer/skin aging alert cancer and early skin aging. This product has been shown only to help prevent sunburn, not skin cancer or early skin aging.

Do not use on damaged or broken skin.

When using this product keep out of eyes. rinse with water to remove.

Stop use and ask doctor if rash occurs.

Keep out of reach of children. If product is swallowed get medical help or contact a poison control center right away.

DOSAGE AND ADMINISTRATION

Apply generously and evenly 15 minutes before sun exposure.
Reapply at least every 2 hours.
Use a water resistant sunscreen if swimming or sweating.
Children under 6 month: ask a doctor.

KEEP OUT OF REACH OF CHILDREN

If product is swallowed get medical help or contact a poison control center right away.

INACTIVE INGREDIENT

MINERAL OIL(PARAFFINUM LIQUIDUM), HYDROGENATED STYRENE/ISOPRENE COPOLYMER, SILICA DIMETHYL SILYLATE, GLYCERYL CAPRYLATE, FRAGRANCE, SIMMONDSIA CHINENSIS (JOJOBA) SEED OIL, SQUALANE, MACADAMIA INTEGRIFOLIA SEED OIL, OLEA EUROPAEA (OLIVE) FRUIT OIL, PENTAERYTHRITYL TETRA-DI-t-BUTYL HYDROXYHYDROCINNAMATE, SYNTHETIC FLUORPHLOGOPITE, MICA, TIN OXIDE, IRON OXIDES(CI 77491), TITANIUM DIOXIDE(CI 77891), FD&C YELLOW NO. 5(CI 19140), FD&C RED NO. 40(CI 16035)